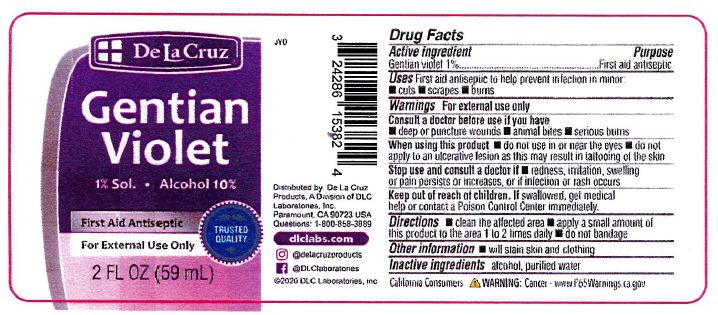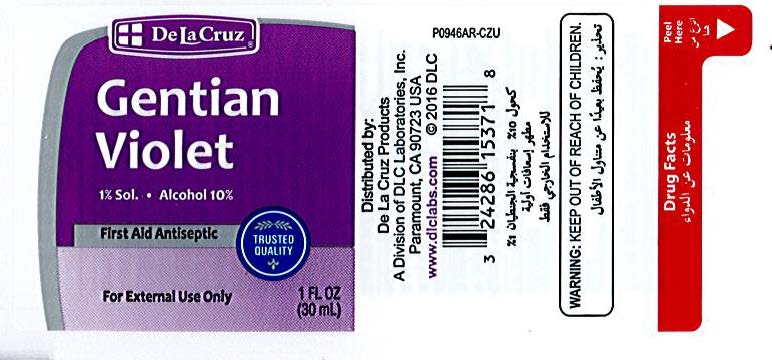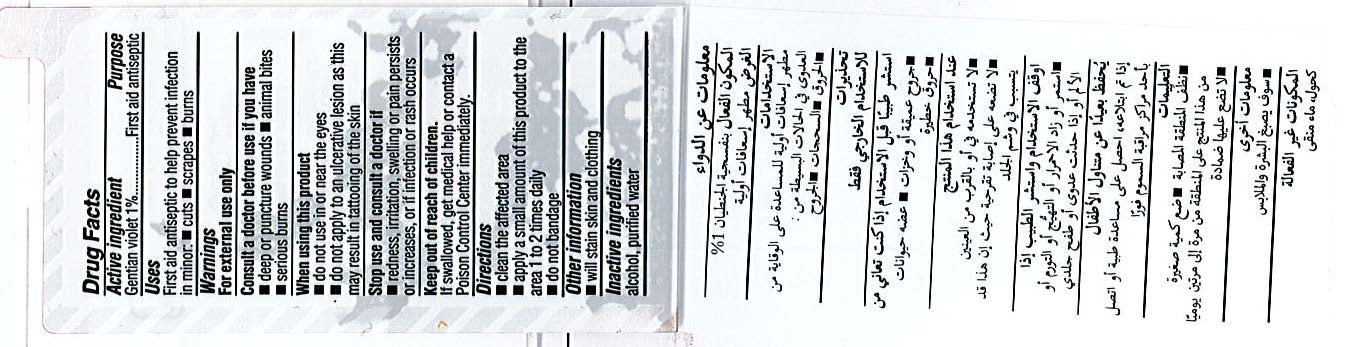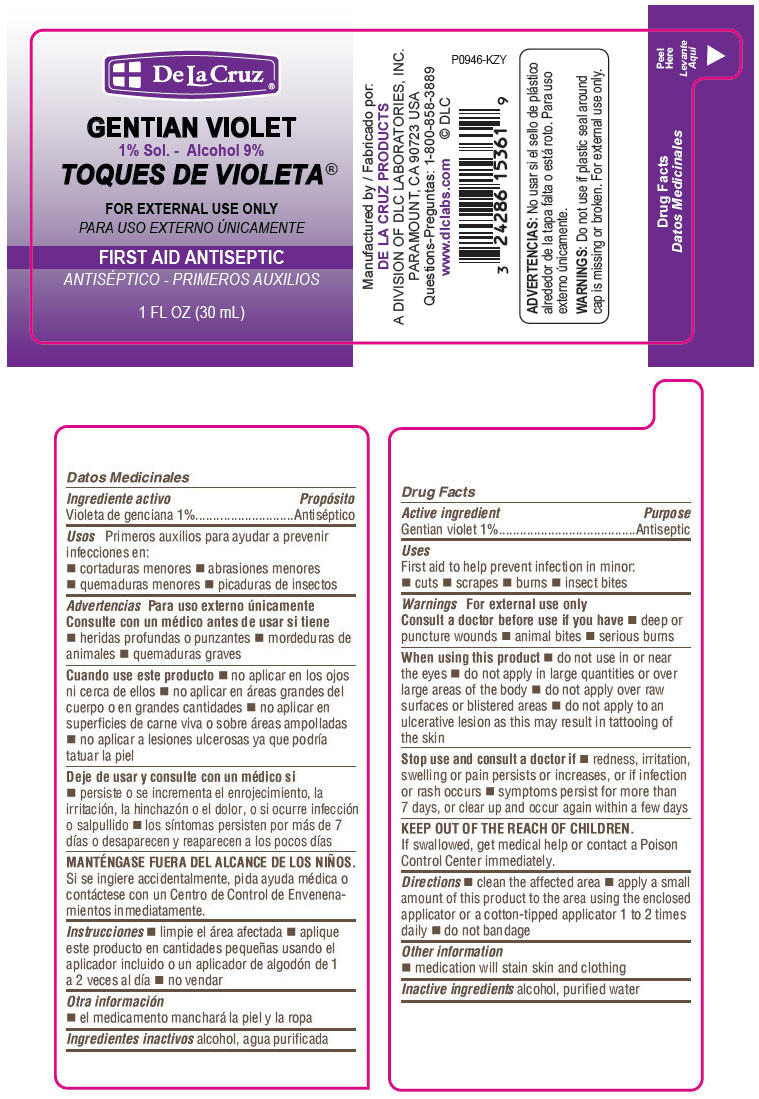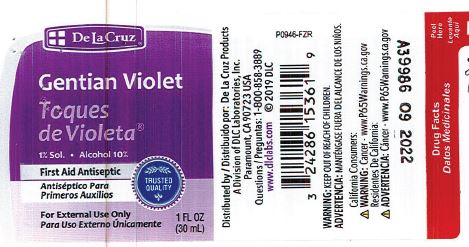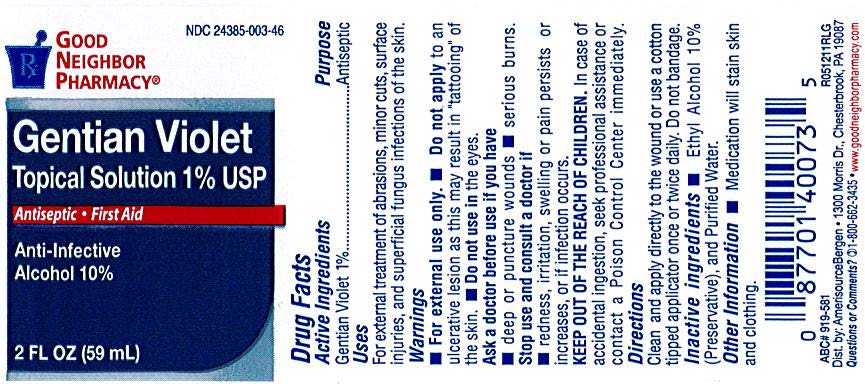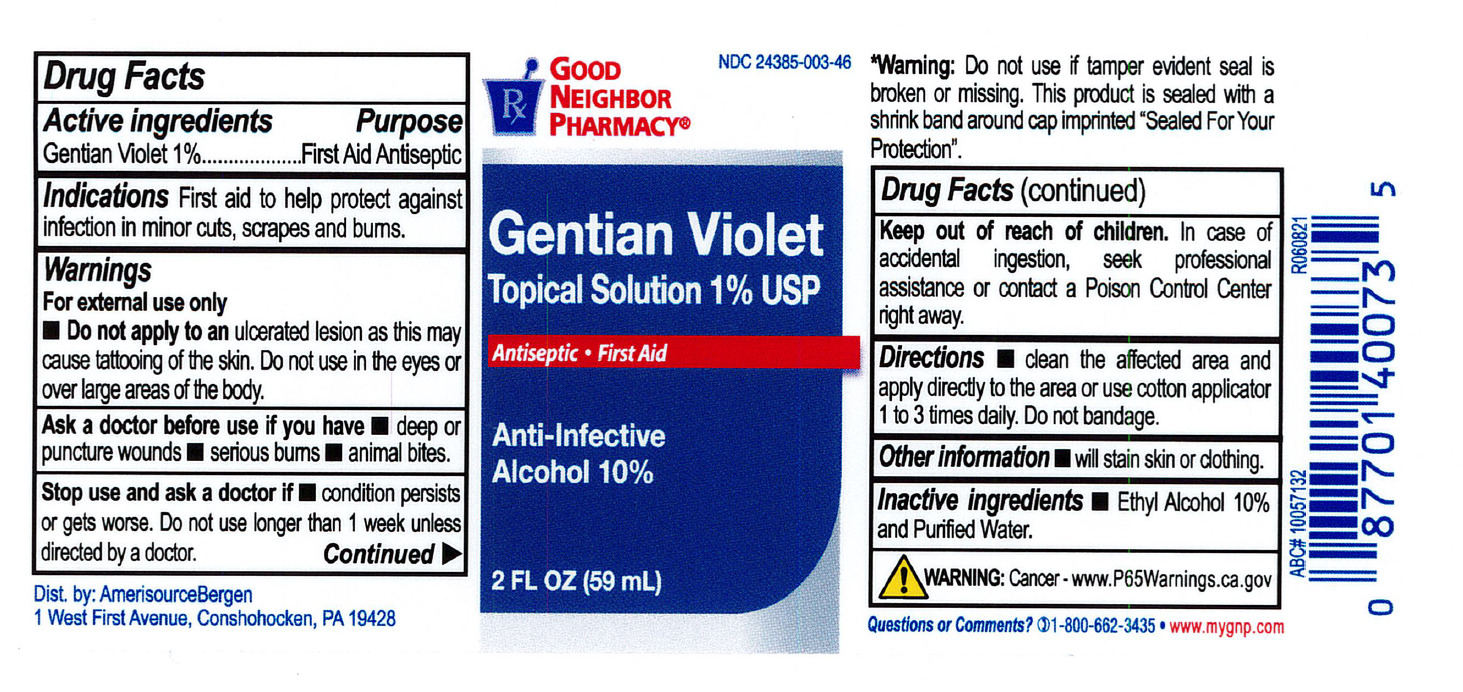 DRUG LABEL: Gentian Violet 1%
NDC: 82645-917 | Form: LIQUID
Manufacturer: Pharma Nobis, LLC
Category: otc | Type: HUMAN OTC DRUG LABEL
Date: 20231226

ACTIVE INGREDIENTS: GENTIAN VIOLET 10 mg/1 mL
INACTIVE INGREDIENTS: ALCOHOL; WATER

Private Label Gentian Violet 1%

Drug facts

Active Ingredient

Gentian Violet 1%

Purpose

Antiseptic

Indications

First aid to help protect against infection in minor cuts, scrapes, and burns.

Indications

First aid to help protect against infection in minor cuts, scrapes, and burns. (12/2021)

Warnings

For external use only.

Do not apply to an ulcerative lesion as this may cause tatooing of the skin. Do not use in the eyes or over large areas of the body.

Ask a doctor before use if

redness, irritation, swelling or pain persists or increases or if infection ocurs.

Keep out of reach of children.

In case of accidental ingestion, seek professional assistance or contact a Poison Control Center right away.

Directions

Clean the affected area and apply directly to the wound or use cotton applicator once or twice daily. Do not bandage.

Other information

will stain skin or clothing.

Inactive ingredients

Ethyl Alcohol 10% and Purified Water.